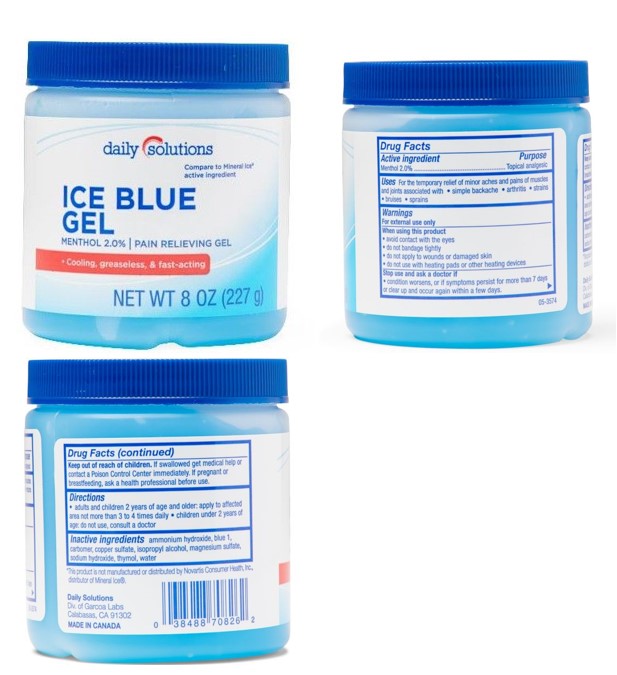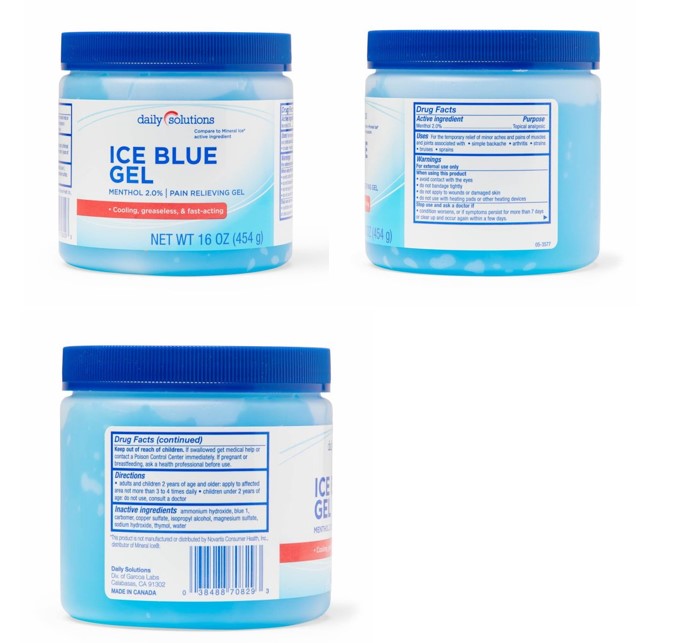 DRUG LABEL: daily solutions Ice Blue
NDC: 67385-708 | Form: GEL
Manufacturer: Garcoa, Inc.
Category: otc | Type: HUMAN OTC DRUG LABEL
Date: 20260206

ACTIVE INGREDIENTS: Menthol, Unspecified Form 20 mg/1 g
INACTIVE INGREDIENTS: AMMONIA; BLUE 1; CARBOMER; CUPRIC SULFATE ANHYDROUS; ISOPROPYL ALCOHOL; MAGNESIUM SULFATE ANHYDROUS; SODIUM HYDROXIDE; THYMOL; WATER

Leader Ice Blue Gel
Topical Analgesic

Drug Facts

Active ingredients

Menthol 2%

Purpose

Topical Analgesic

Uses

For the temporary relief of minor aches and pains of muscles and joints associated with • simple backache •arthritis •strains • bruises • sprains

Warnings

For external use only

When using this product

- avoid contact with the eyes
- do not bandage tightly
- do not apply to wounds or damaged skin
- do not use with heating pads or other heating devices

Stop use and ask a doctor if

- condition worsens, or if symptoms persist for more than 7 days or clear up and occur again within a few days.

If pregnant or breastfeeding, ask a health professional before use

Keep out of reach of children. If swallowed, get medical help or contact a Poison Control Center (1-800-222-1222) immediately.

Directions

- adults and children 2 years of age and older: apply to affected area not more than 3 to 4 times daily
- children under 2 years of age: do not use, consult a doctor

Inactive ingredients

Ammonium Hydroxide, Blue 1, Carbomer, Copper Sulfate, Isopropyl Alcohol, Magnesium Sulfate, Sodium Hydroxide, Thymol, Water.

Questions or comments?

1-866-567-8600

Daily Solutions

Div. of Garcoa Labs

Calabasas, CA 91302

PRINCIPAL DISPLAY PANEL - 226.8 g Jar Label

Daily Solutions

Ice Blue Gel
Menthol 2.0% Pain Relieving Gel

Cooling, greaseless

+fast-acting

COMPARE TO
MINERAL ICE®
active ingredient*

NET WT 8 OZ (227g)

8 oz Ice Blue

PDP 454g jar label

Daily Solutions

Menthol 2.0%

Ice Blue Gel

Pain Relieving Gel

Cooling, greaseless

+fast-acting

COMPARE TO
MINERAL ICE®
active ingredient*

NET WT 16 OZ (454g)

16 oz Ice Blue